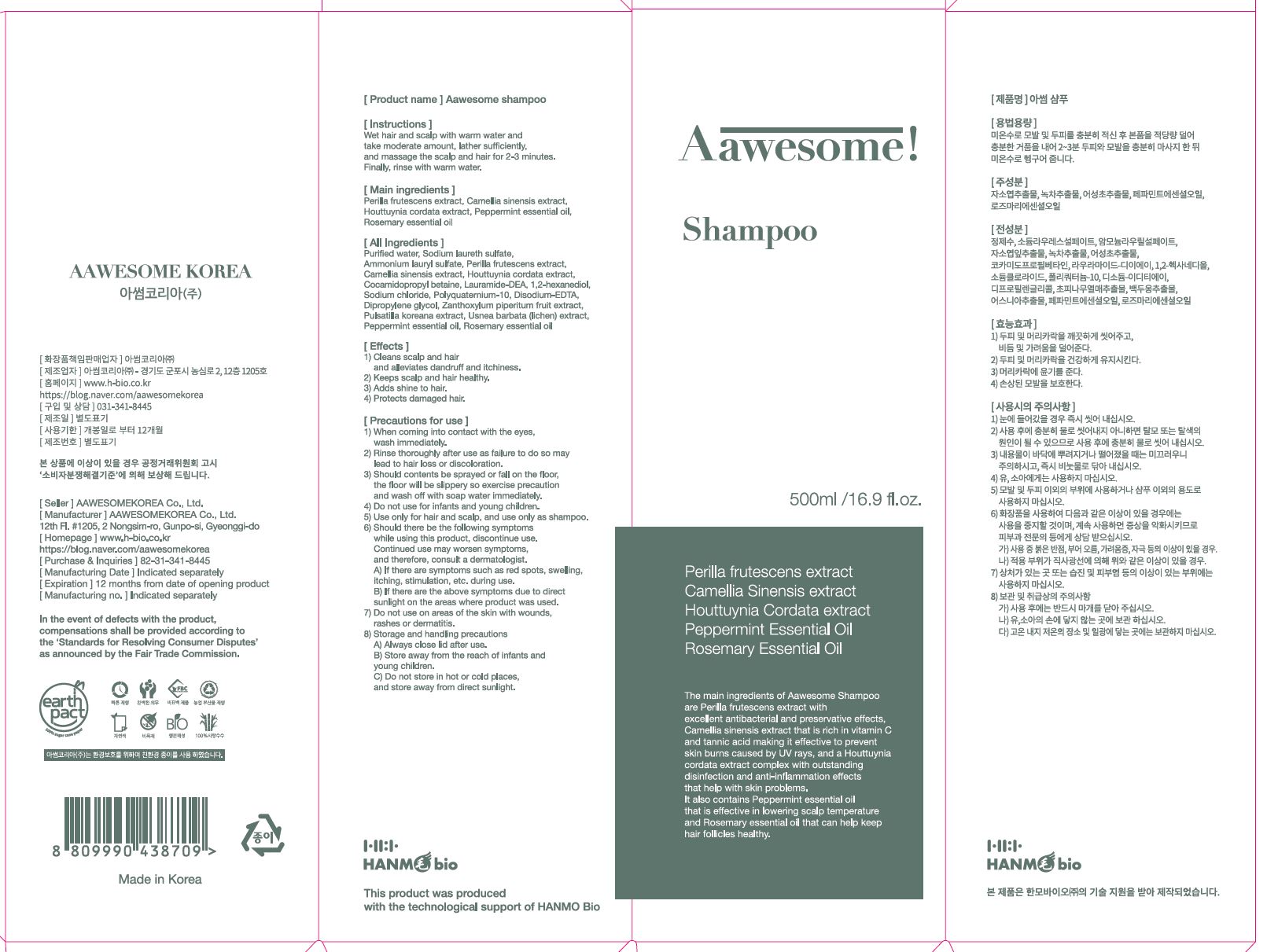 DRUG LABEL: AAWESOMEshampoo
NDC: 82483-0001 | Form: SHAMPOO
Manufacturer: AAWESOMEKOREA Co., Ltd.
Category: otc | Type: HUMAN OTC DRUG LABEL
Date: 20220121

ACTIVE INGREDIENTS: CAMELLIA SINENSIS WHOLE 5.91 g/100 mL; PEPPERMINT OIL 0.5 g/100 mL; PERILLA FRUTESCENS WHOLE 5.91 g/100 mL; HOUTTUYNIA CORDATA WHOLE 5.914 g/100 mL; ROSEMARY OIL 0.5 g/100 mL
INACTIVE INGREDIENTS: WATER

ACTIVE INGREDIENT

CAMELLIA SINENSIS, PEPPERMINT, ROSEMARY, PERILLA FRUTESCENS, HOUTTUYNIA CORDATA

PURPOSE

cleans scalp and hair and alleviates dandruff and itchiness

keeps scalp and hair healthy

adds shin to hair

protects damaged hair

KEEP OUT OF REACH OF THE CHILDREN

WARNINGS

■ For external use only.

■ Do not use in eyes.

■ lf swallowed, get medical help promptly.

■ Stop use, ask doctor lf irritation occurs.

■ Keep out of reach of children.

DOSAGE AND ADMINISTRATION

for external use only

INACTIVE INGREDIENT

water, sodium laureth sulfate, etc

INDICATIONS AND USAGE

combine hair before shampoo to remove large dust

gently massage shampoo into wet hair and scalp all over your tips

rinse to remove any remaining dubbles

tap wet hair with a toweland let it dry in natural or cold wind